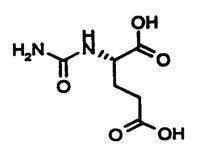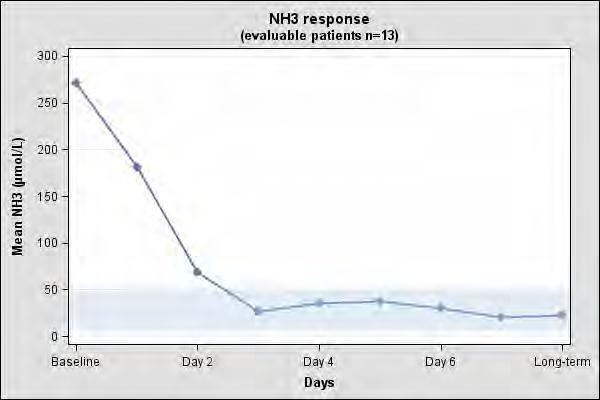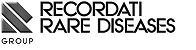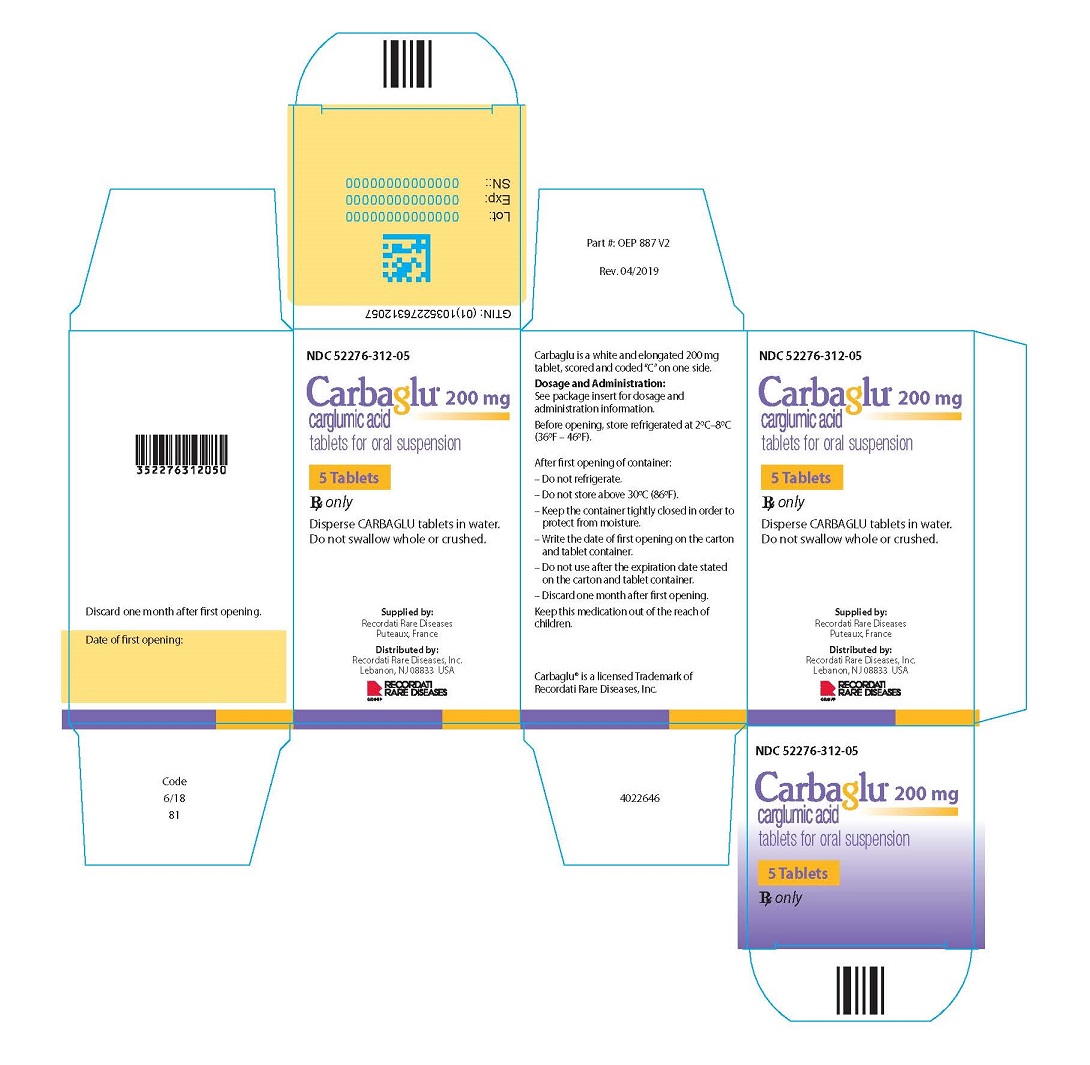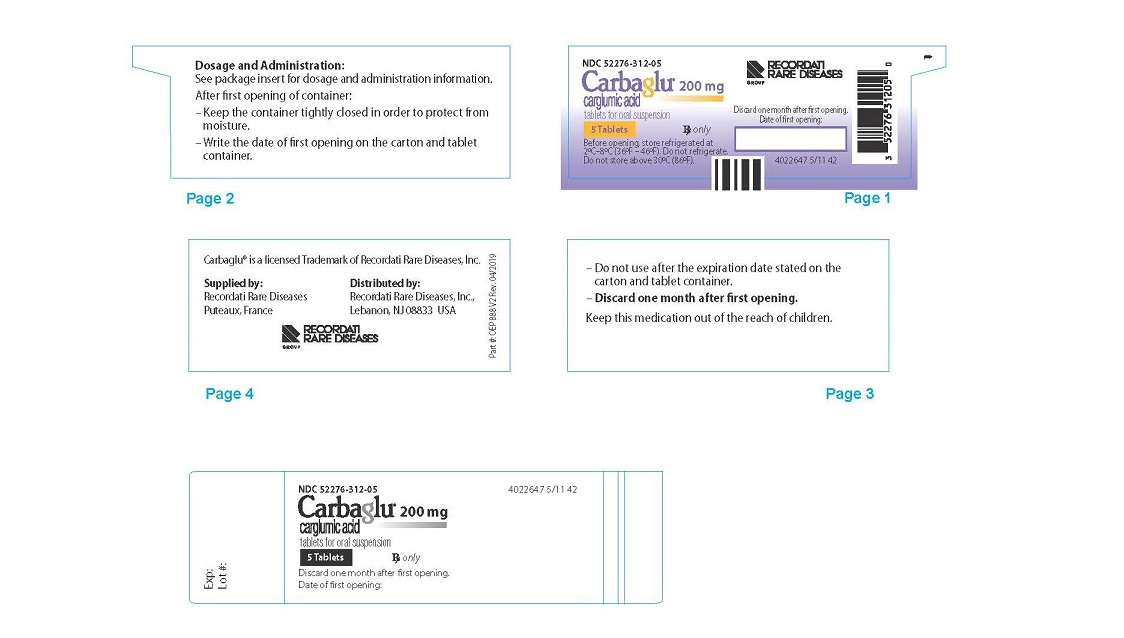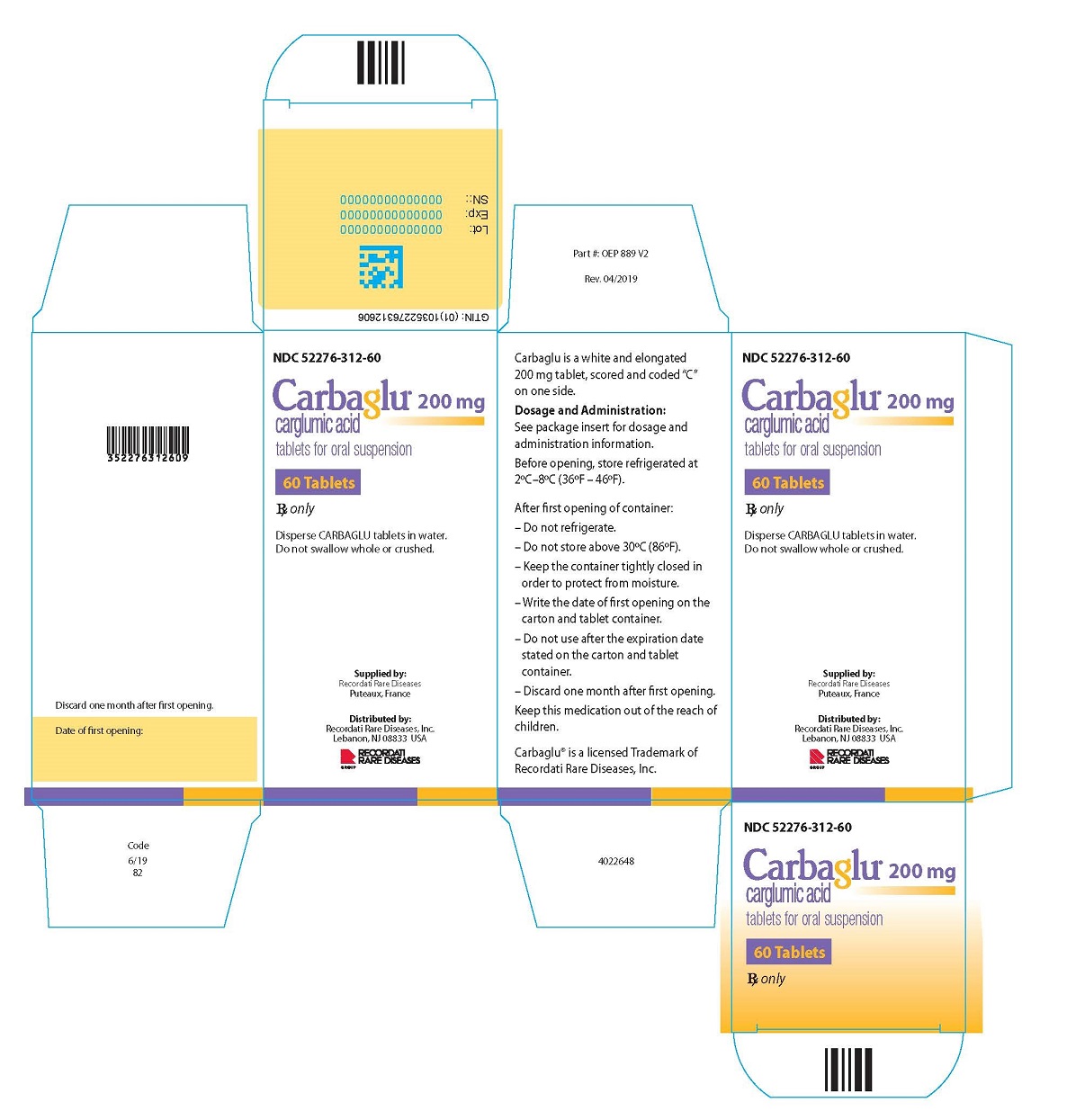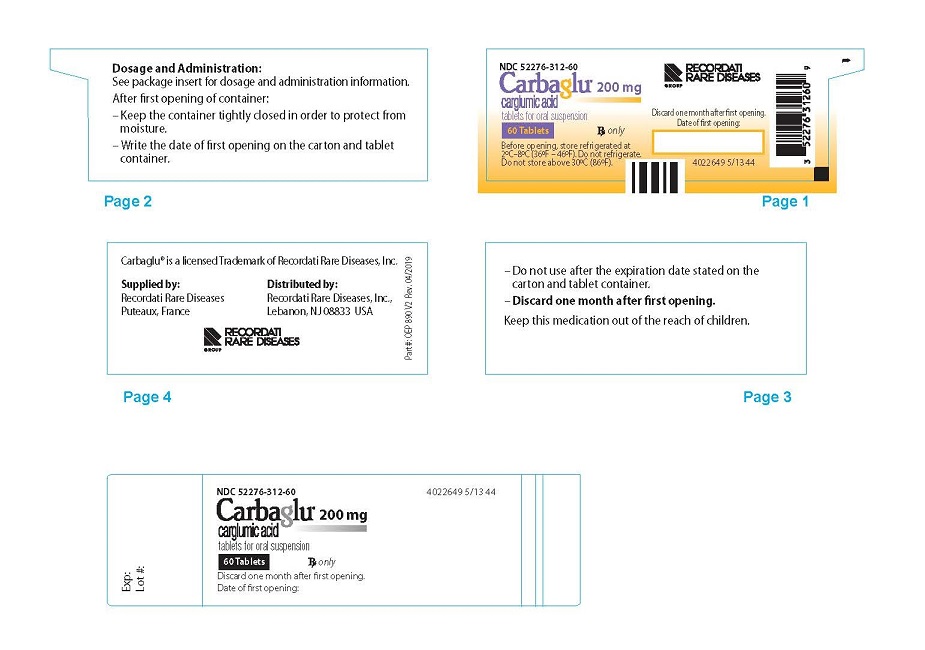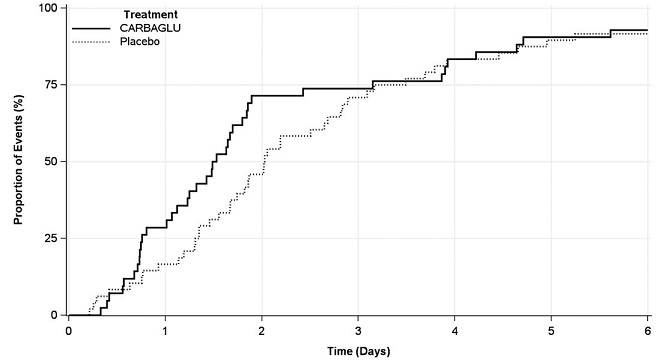 DRUG LABEL: Carbaglu
NDC: 52276-312 | Form: TABLET, FOR SUSPENSION
Manufacturer: Recordati Rare Diseases
Category: prescription | Type: HUMAN PRESCRIPTION DRUG LABEL
Date: 20240125

ACTIVE INGREDIENTS: CARGLUMIC ACID 200 mg/1 1
INACTIVE INGREDIENTS: MICROCRYSTALLINE CELLULOSE; SODIUM LAURYL SULFATE; HYPROMELLOSE, UNSPECIFIED; CROSCARMELLOSE SODIUM; SILICON DIOXIDE; SODIUM STEARYL FUMARATE

HIGHLIGHTS OF PRESCRIBING INFORMATION

These highlights do not include all the information needed to use CARBAGLU safely and effectively. See full prescribing information for CARBAGLU.
Carbaglu® (carglumic acid) tablets for oral suspension
Initial U.S. Approval: 2010

1. INDICATIONS AND USAGE

CARBAGLU is a carbamoyl phosphate synthetase 1 (CPS 1) activator indicated in pediatric and adult patients as:

- Adjunctive therapy to standard of care for the treatment of acute hyperammonemia due to N-acetylglutamate synthase (NAGS) deficiency. (1.1)
- Maintenance therapy for the treatment of chronic hyperammonemia due to NAGS deficiency. (1.1)
- Adjunctive therapy to standard of care for the treatment of acute hyperammonemia due to propionic acidemia (PA) or methylmalonic acidemia (MMA). (1.2)

2. DOSAGE AND ADMINISTRATION

Acute Hyperammonemia due to NAGS deficiency (2.2)

- The recommended dosage in adult and pediatric patients is 100 mg/kg to 250 mg/kg orally daily. Divide the daily dosage into 2 to 4 doses.

Chronic Hyperammonemia due to NAGS deficiency (2.2)

- The recommended dosage in adult and pediatric patients is 10 mg/kg to 100 mg/kg orally daily. Divide the daily dosage into 2 to 4 doses.

Therapeutic Monitoring for NAGS Deficiency (2.2)

- Closely monitor plasma ammonia and titrate dosage to maintain the ammonia level within normal range for the patient's age, taking into consideration their clinical condition.

Acute Hyperammonemia due to PA or MMA (2.3)

- The recommended dosage in adult and pediatric patients is:
  - 150 mg/kg orally daily for patients less than or equal to 15 kg
  - 3.3 g/m^2 orally daily for patients greater than 15 kg
- Divide the daily dosage into 2 doses.
- Continue treatment until ammonia level is less than 50 micromol/L and for a maximum duration of 7 days.

Patients with Renal Impairment (2.4)

- See Full Prescribing Information for Instructions on Dosage Adjustment.

Preparation and Administration (2.5)

- Disperse CARBAGLU tablets in water. Do not swallow whole or crushed.
- Take immediately before meals or feedings.
- For additional instructions on preparation and administration orally or through a nasogastric tube or gastrostomy tube, see Full Prescribing Information.

3. DOSAGE FORMS AND STRENGTHS

Tablets for oral suspension: 200 mg, functionally scored. (3)

4. CONTRAINDICATIONS

None. (4)

6. ADVERSE REACTIONS

- NAGS deficiency: Most common adverse reactions (≥13%) are vomiting, abdominal pain, pyrexia, tonsillitis, anemia, diarrhea, ear infection, infections, nasopharyngitis, hemoglobin decreased, and headache. (6.1)
- PA and MMA: Most common adverse reactions (≥5%) are neutropenia, anemia, vomiting, electrolyte imbalance, decreased appetite, hypoglycemia, lethargy/stupor, encephalopathy and pancreatitis/lipase increased. (6.1)

To report SUSPECTED ADVERSE REACTIONS, contact Recordati Rare Diseases Inc. at 1-888-575-8344, or FDA at 1-800-FDA-1088 or www.fda.gov/medwatch.

FULL PRESCRIBING INFORMATION

1. INDICATIONS AND USAGE

1.1 Acute and Chronic Hyperammonemia due to N‑acetylglutamate Synthase (NAGS) Deficiency

CARBAGLU is indicated in adult and pediatric patients as:

- Adjunctive therapy to standard of care for the treatment of acute hyperammonemia due to NAGS deficiency.
- Maintenance therapy for the treatment of chronic hyperammonemia due to NAGS deficiency.

1.2 Acute Hyperammonemia due to Propionic Acidemia (PA) or Methylmalonic Acidemia (MMA)

CARBAGLU is indicated in adult and pediatric patients as adjunctive therapy to standard of care for the treatment of acute hyperammonemia due to PA or MMA.

2. DOSAGE AND ADMINISTRATION

2.1 Important Administration Instructions

- Disperse CARBAGLU tablets in water. Do not swallow whole or crush [see Dosage and Administration (2.5)].
- CARBAGLU may be administered by mouth or via a nasogastric or gastrostomy tube [see Dosage and Administration (2.5)].

2.2 Recommended Dosage for Acute or Chronic Hyperammonemia due to NAGS Deficiency

Treatment Initiation
Initiate CARBAGLU treatment as soon as the diagnosis of NAGS deficiency is suspected, which may be as soon as at birth, and supervised by a healthcare provider experienced in the treatment of metabolic disorders.

Dosage for Acute Hyperammonemia due to NAGS Deficiency

- The recommended dosage of CARBAGLU in adult and pediatric patients for acute hyperammonemia due to NAGS deficiency is (based on actual body weight) 100 mg/kg to 250 mg/kg orally daily.
- Divide the daily dosage into 2 to 4 doses and round to the nearest 100 mg (i.e., half of a CARBAGLU tablet).
- During acute hyperammonemic episodes, administer CARBAGLU with other ammonia lowering therapies, such as alternate pathway medications, hemodialysis, and protein restriction.

Dosage for Chronic Hyperammonemia due to NAGS Deficiency

- The recommended dosage of CARBAGLU in adult and pediatric patients for chronic hyperammonemia due to NAGS deficiency is (based on actual body weight) 10 mg/kg to 100 mg/kg orally daily.
- Divide the daily dosage into 2 to 4 doses and round to the nearest 100 mg (i.e., half of a CARBAGLU tablet).
- During maintenance therapy, the concomitant use of other ammonia lowering therapies and protein restriction may be needed based on plasma ammonia levels.

Therapeutic Monitoring
Closely monitor plasma ammonia levels. Titrate the CARBAGLU dosage to maintain the plasma ammonia level within the normal range for the patient's age, taking into consideration their clinical condition (e.g., nutritional requirements, protein intake, growth parameters, etc.).

Adjust the recommended dosage in patients with moderate or severe renal impairment [see Dosage and Administration (2.4)].

2.3 Recommended Dosage for Acute Hyperammonemia due to PA or MMA

Treatment Initiation
Initiate CARBAGLU for the treatment of acute hyperammonemia in patients with a suspected or confirmed diagnosis of PA or MMA.

Dosage for Acute Hyperammonemia due to PA or MMA

- The recommended dosage of CARBAGLU in adult and pediatric patients with acute hyperammonemia due to PA or MMA is (based on actual body weight):
  - 150 mg/kg orally daily for patients less than or equal to 15 kg
  - 3.3 g/m^2 orally daily for patients greater than 15 kg
- Divide the daily dosage into 2 equal doses and round up to the nearest 50 mg (i.e., one-quarter of a CARBAGLU tablet). Administer doses 12 hours apart.
- Continue CARBAGLU treatment until the patient's ammonia level is less than 50 micromol/L and for a maximum duration of 7 days.
- During acute hyperammonemic episodes, administer CARBAGLU with other ammonia lowering therapies, such as intravenous glucose, insulin, L-carnitine, protein restriction, and dialysis.

Adjust the recommended dosage in patients with moderate or severe renal impairment [see Dosage and Administration (2.4)].

2.4 Dosage Adjustment in Patients with Renal Impairment

No dosage adjustment is warranted in patients with mild renal impairment (eGFR 60-89 mL/min/1.73 m^2). The recommended dosage of CARBAGLU in patients with moderate or severe renal impairment is shown below.

 | Moderate Renal Impairment (eGFR 30-59 mL/min/1.73 m^2) | Severe Renal Impairment (eGFR 15-29 mL/min/1.73 m^2)
Acute Hyperammonemia due to NAGS Deficiency | 50 mg/kg/day to 125 mg/kg/day divided into 2 to 4 doses and rounded to the nearest 50 mg (i.e., one-quarter of a CARBAGLU tablet) | 15 mg/kg/day to 60 mg/kg/day divided into 2 to 4 doses and rounded to the nearest 50 mg (i.e., one-quarter of a CARBAGLU tablet)
Chronic Hyperammonemia due to NAGS Deficiency | 5 mg/kg/day to 50 mg/kg/day divided into 2 to 4 doses and rounded to the nearest 50 mg (i.e., one-quarter of a CARBAGLU tablet) | 2 mg/kg/day to 25 mg/kg/day divided into 2 to 4 doses and rounded to the nearest 50 mg (i.e., one-quarter of a CARBAGLU tablet)
Acute Hyperammonemia due to PA or MMA | - 75 mg/kg/day for patients weighing ≤ 15 kg - 1.7 g/m^2/day for patients weighting > 15 kg; Divide daily dosage into 2 equal doses and round up to the nearest 50 mg (i.e., one-quarter of a CARBAGLU tablet); administer each dose 12 hours apart. | - 25 mg/kg/day for patients weighing ≤ 15 kg - 0.55 g/m^2/day for patients weighting > 15 kg; Divide daily dosage into 2 equal doses and round up to the nearest 50 mg (i.e., one-quarter of a CARBAGLU tablet); administer each dose 12 hours apart.

2.5 Preparation and Administration

Overview

- Disperse CARBAGLU tablets in water. Do not swallow whole or crush.
- CARBAGLU tablets do not dissolve completely in water, and undissolved particles of the tablet may remain in the mixing container.
- Take CARBAGLU immediately before meals or feedings.
- The CARBAGLU suspension has a slightly acidic taste.
- For all preparations, use in foods or liquids other than water has not been studied and is not recommended.

Oral Administration
For oral administration, administer CARBAGLU as follows:

- Add a minimum of 2.5 mL of water into a small cup for each CARBAGLU tablet or each ½ or ¼ CARBAGLU tablet needed for the prescribed dose.
- Add the CARBAGLU tablets to the water in the cup.
- Carefully stir the tablet and water mixture.
- Swallow the mixture immediately. Pieces of the tablet may remain in the cup.
- Rinse the cup with additional water and swallow the mixture immediately. Repeat as needed until no pieces of the tablet are left in the cup.

Use of an Oral Syringe for Oral Administration
For administration via an oral syringe, administer CARBAGLU as follows:

- Add a minimum of 2.5 mL of water into a small cup for each CARBAGLU tablet or each ½ or ¼ CARBAGLU tablet needed for the prescribed dose.
- Add the CARBAGLU tablets to the water in the cup.
- Carefully stir the tablet and water mixture.
- Draw up the mixture in an oral syringe and administer immediately. Pieces of the tablet may remain in the oral syringe.
- Refill the oral syringe with a minimum volume of water (1 mL to 2 mL) and administer immediately.
- Flush the oral syringe again, as needed, until no pieces of the tablet are left in the syringe.

Use of Nasogastric Tube (NG Tube) or Gastrostomy Tube (G-Tube) for Feeding Tube Administration

For patients who have a NG tube or G-tube in place, administer CARBAGLU as follows:

- Add a minimum of 2.5 mL of water into a small cup for each CARBAGLU tablet or each ½ or ¼ CARBAGLU tablet needed for the prescribed dose.
- Add the CARBAGLU tablets to the water in the cup.
- Carefully stir the tablet and water mixture.
- Draw up the mixture into a catheter-tip syringe.
- Administer the mixture immediately through the NG tube or G-tube. Pieces of the tablet may remain in the catheter-tip syringe or the feeding tube.
- Flush immediately with 1 to 2 mL of additional water to clear the NG tube or G-tube.
- Flush the NG tube or G-tube again, as needed, until no pieces of the tablet are left in the syringe or the feeding tube.

3. DOSAGE FORMS AND STRENGTHS

Tablets for oral suspension: 200 mg of carglumic acid, white, elongated, functionally scored with 3 lines (for splitting into 4 equal portions) and printed "C" on one side.

4. CONTRAINDICATIONS

None

6. ADVERSE REACTIONS

6.1 Clinical Trials Experience

Because clinical trials are conducted under widely varying conditions, adverse reaction rates observed in the clinical trials of a drug cannot be directly compared to rates in the clinical trials of another drug and may not reflect the rates observed in practice.

Acute and Chronic Hyperammonemia due to NAGS Deficiency
In a retrospective case series of 23 NAGS deficiency patients treated with CARBAGLU, 17 of the 23 patients reported an adverse reaction. The most common adverse reactions (occurring in ≥ 13% of patients) were vomiting, abdominal pain, pyrexia, tonsillitis, anemia, diarrhea, ear infection, infections, nasopharyngitis, hemoglobin decreased, and headache.

Table 1 summarizes adverse reactions occurring in 2 or more patients treated with CARBAGLU.

Table 1: Adverse Reactions Reported in ≥ 2 Patients with NAGS deficiency Treated with CARBAGLU in the Retrospective Case Series
Adverse Reaction | Number of Patients (N) (%)
Vomiting | 6 (26)
Abdominal pain | 4 (17)
Pyrexia | 4 (17)
Tonsillitis | 4 (17)
Anemia | 3 (13)
Diarrhea | 3 (13)
Ear infection | 3 (13)
Infections | 3 (13)
Nasopharyngitis | 3 (13)
Hemoglobin decreased | 3 (13)
Headache | 3 (13)
Dysgeusia | 2 (9)
Asthenia | 2 (9)
Hyperhidrosis | 2 (9)
Influenza | 2 (9)
Pneumonia | 2 (9)
Weight decreased | 2 (9)
Anorexia | 2 (9)
Somnolence | 2 (9)
Rash | 2 (9)

Acute Hyperammonemia due to PA and MMA
In a randomized, double-blind, placebo-controlled clinical trial, 24 patients (15 with PA and 9 with MMA) experienced a total of 90 hyperammonemic episodes which were randomized 1:1 to be treated with either CARBAGLU or placebo, each in addition to standard-of-care therapy, with randomization based on each hyperammonemic episode. The average patient age (SD) was 9.2 years (7.7) and 12 (50 %) were males.

CARBAGLU was administered at a dosage of 150 mg/kg/day for patients ≤15 kg or 3.3 g/m^2/day for patients >15 kg, divided into 2 doses, for a median duration of 4.14 days.

At least 1 adverse reaction was reported during the course of hyperammonemic episodes in 42% of hyperammonemic episodes. The most common adverse reactions (≥5%) during hyperammonemic episodes were neutropenia, anemia, vomiting, electrolyte imbalance, decreased appetite, hypoglycemia, lethargy/stupor, encephalopathy and pancreatitis/lipase increased.

Table 2 summarizes adverse reactions (≥2%) during hyperammonemic episodes in patients with PA or MMA treated with CARBAGLU or placebo.

Table 2: Adverse Reactions (≥ 2%) During Hyperammonemic Episodes in Patients with PA or MMA Treated with CARBAGLU or Placebo
Adverse Reaction | Treatment Arm
Adverse Reaction | CARBAGLU N=42 episodes | PLACEBO N=48 episodes
Adverse Reaction | N (%) | N (%)
Neutropenia | 6 (14) | 4 (8)
Anemia | 5 (12) | 4 (8)
Vomiting | 3 (7) | 1 (2)
Electrolyte imbalance | 3 (7) | 2 (4)
Decreased appetite | 2 (5) | 1 (2)
Hypoglycemia | 2 (5) | 1 (2)
Lethargy/Stupor | 2 (5) | 1 (2)
Encephalopathy | 2 (5) | 0 (0)
Pancreatitis/Lipase increased | 2 (5) | 0 (0)
Cardiomyopathy | 1 (2) | 0 (0)
Alanine aminotransferase increased | 1 (2) | 0 (0)
Aspartate aminotransferase increased | 1 (2) | 0 (0)
Infusion site extravasation | 1 (2) | 0 (0)
White blood cell count increased | 1 (2) | 0 (0)
Behavior disorder | 1 (2) | 0 (0)
Sleep disorder | 1 (2) | 0 (0)
Apnea | 1 (2) | 0 (0)
Hyperventilation | 1 (2) | 0 (0)

6.2 Postmarketing Experience

The following adverse reactions have been identified during postapproval use of CARBAGLU. Because these reactions are reported voluntarily from a population of uncertain size, it is not always possible to reliably estimate their frequency or to establish a causal relationship to drug exposure.

Psychiatric disorders: mania

Skin and subcutaneous tissue disorders: pruritus, rash including rash erythematous, rash maculopapular, rash pustular

8. USE IN SPECIFIC POPULATIONS

8.1 Pregnancy

Pregnancy Exposure Registry
There is a pregnancy exposure registry that monitors pregnancy outcomes in women with NAGS deficiency exposed to CARBAGLU. If CARBAGLU is administered during pregnancy, health care providers should report CARBAGLU exposure by calling 1-888-575-8344.

Risk Summary
Although rare case reports of CARBAGLU use in pregnant women are insufficient to inform a drug-associated risk of major birth defects, miscarriage, or adverse maternal or fetal outcomes, untreated NAGS deficiency, PA and MMA can result in irreversible neurologic damage and death in pregnant women (see Clinical Considerations).

In an animal reproduction study, decreased survival and growth occurred in offspring born to rats that received carglumic acid at a dose approximately 38 times the maximum reported human maintenance dose.

The estimated background risk of major birth defects and miscarriage for the indicated population is unknown. All pregnancies have a background risk of birth defect, miscarriage, or other adverse outcomes. In the U.S. general population, the estimated background risk of major birth defects and miscarriage in clinically recognized pregnancies is 2% to 4% and 15% to 20%, respectively.

Clinical Considerations
Disease-associated maternal and/or embryo/fetal risk
Pregnant women with urea cycle disorders, PA, and MMA may experience an increase in catabolic stress which can trigger a hyperammonemic crisis both in the intrapartum and in the post-partum (3-14 days post-partum) periods. Maternal complications related to hyperammonemic crisis can include neurological impairment, coma and in some cases death.

Data
Animal Data
No effects on embryo-fetal development were observed in pregnant rats treated with up to 2000 mg/kg/day (approximately 38 times the maximum reported human maintenance dose [100 mg/kg/day] based on AUC [area under the plasma concentration-time curve]) from two weeks prior to mating through organogenesis or in pregnant rabbits treated with up to 1000 mg/kg/day (approximately 6 times the maximum reported human maintenance dose [100 mg/kg/day] based on AUC) during organogenesis.

In a pre- and post-natal developmental study, female rats received oral carglumic acid from organogenesis through lactation at doses of 500 mg/kg/day and 2000 mg/kg/day. Decreased growth of offspring was observed at 500 mg/kg/day and higher (approximately 38 times the maximum reported human maintenance dose [100 mg/kg/day] based on AUC), and reduction in offspring survival during lactation was observed at 2000 mg/kg/day (approximately 38 times the maximum reported human maintenance dose [100 mg/kg/day] based on AUC). No effects on physical and sexual development, learning and memory, or reproductive performance were observed through maturation of the surviving offspring at maternal doses up to 2000 mg/kg/day. The high dose (2000 mg/kg/day) produced maternal toxicity (impaired weight gain and approximately 10% mortality).

8.2 Lactation

Risk Summary
It is not known whether carglumic acid is present in human milk. There are no available data on the effects of carglumic acid on the breastfed infant or the effects on milk production. Carglumic acid is present in milk from treated rats. When a drug is present in animal milk, it is likely that the drug will be present in human milk.

The developmental and health benefits of breastfeeding should be considered along with the mother's clinical need for CARBAGLU and any potential adverse effects on the breastfed child from CARBAGLU or from the underlying maternal condition.

8.4 Pediatric Use

The safety and effectiveness of CARBAGLU for the treatment of pediatric patients (birth to 17 years of age) with acute or chronic hyperammonemia due to NAGS deficiency and acute hyperammonemia due to PA or MMA have been established, and the information on these uses are discussed throughout the labeling. There are insufficient data to determine if there is a difference in clinical or biochemical responses between adult and pediatric patients treated with CARBAGLU.

8.5 Geriatric Use

Clinical studies of CARBAGLU did not include patients 65 years of age and older to determine whether they respond differently from younger patients.

8.6 Renal Impairment

Plasma concentrations of carglumic acid increased in patients with renal impairment [see Clinical Pharmacology (12.3)]. Reduce the CARBAGLU dosage in patients with moderate or severe renal impairment [see Dosage and Administration (2.4)]. The pharmacokinetics of carglumic acid have not been evaluated in patients with end stage renal disease.

10. OVERDOSAGE

One patient treated with 650 mg/kg/day of CARBAGLU developed symptoms resembling monosodium glutamate intoxication-like syndrome and characterized by tachycardia, profuse sweating, increased bronchial secretions, increased body temperature, and restlessness. These symptoms resolved upon reduction of the dose.

11. DESCRIPTION

CARBAGLU tablets for oral suspension contain 200 mg of carglumic acid. Carglumic acid, the active substance, is a carbamoyl phosphate synthetase 1 (CPS 1) activator and is soluble in boiling water, slightly soluble in cold water, and practically insoluble in organic solvents.

The chemical name of carglumic acid is N-carbamoyl-L-glutamic acid or (2S)-2-(carbamoylamino) pentanedioic acid. The empirical formula is C6H10N2O5 and the molecular weight is 190.16.

The structural formula is:

The inactive ingredients of CARBAGLU are croscarmellose sodium, hypromellose, microcrystalline cellulose, silica colloidal anhydrous, sodium lauryl sulfate, and sodium stearyl fumarate.

12. CLINICAL PHARMACOLOGY

12.1 Mechanism of Action

Carglumic acid is a synthetic structural analogue of N-acetylglutamate (NAG) which is produced from glutamate and acetyl-CoA in a reaction catalyzed by N‑acetylglutamate synthase (NAGS), a mitochondrial liver enzyme. NAG acts as the essential allosteric activator of carbamoyl phosphate synthetase 1 (CPS 1), a mitochondrial liver enzyme which catalyzes the first reaction of the urea cycle. The urea cycle, whose role is the disposition of ammonia, includes a series of biochemical reactions in the liver resulting in the conversion of ammonia into urea, which is then excreted through the urine. Carglumic acid acts as a CPS1 activator, improves or restores the function of the urea cycle, and facilitates ammonia detoxification and urea production.

12.2 Pharmacodynamics

In a retrospective review of the clinical course in 23 patients with NAGS deficiency, carglumic acid reduced plasma ammonia levels within 24 hours when administered with and without concomitant ammonia lowering therapies. No dose-response relationship has been identified.

Cardiac Electrophysiology
The effect of carglumic acid was evaluated in a Phase 1, randomized study in 76 healthy volunteers. The study suggests a lack of clinically relevant QT prolongation effect at the highest therapeutic dose level (250 mg/kg/day).

12.3 Pharmacokinetics

The pharmacokinetics of carglumic acid in healthy subjects following an intravenous (IV) infusion over 2 hours at 8 mg/kg or an oral administration at 100 mg/kg are summarized in Table 3.

Table 3: Mean (SD) Pharmacokinetic Parameter Values of Carglumic Acid in Healthy Subjects
PK parameter | IV infusion 8 mg/kg (N=10) | Oral 100 mg/kg (N=12)
Cmax (ng/mL) | 8613 (558) | 3284 (321)
Tmax (hr)# | 2 (1-2) | 3 (2-4)
AUC (ng*hr/mL) | 24501 (1613) | 31426 (2150)
T½ (hr) | 31 (3) | 25 (2)
CL (L/hr/kg) | 0.34 (0.02) | N/A
Vd (L/kg) | 15 (1) | N/A
# Median (range); N/A, not applicable

Absorption
Following an oral administration of CARBAGLU 100 mg/kg in healthy subjects, the absolute bioavailability was approximately 10%.

Distribution
Carglumic acid is not bound to plasma proteins.

Elimination
Carglumic acid is predominantly excreted by the kidneys as unchanged product.

Metabolism
A proportion of carglumic acid may be metabolized by the intestinal bacterial flora.

The likely end product of carglumic acid metabolism is carbon dioxide, eliminated through the lungs.

Excretion
Following an oral administration of radiolabeled CARBAGLU at 100 mg/kg, 9% of the dose is excreted unchanged in the urine and up to 60% of the dose is recovered unchanged in the feces.

Specific Populations

Patients with Renal Impairment

The pharmacokinetics of carglumic acid in subjects with renal impairment were compared with healthy subjects with normal renal function following oral administration of a single dose of CARBAGLU 40 mg/kg or 80 mg/kg. The Cmax and AUC0-t of carglumic acid are summarized in Table 4. The geometric mean ratio (90% CI) of Cmax in subjects with mild, moderate, and severe renal impairment relative to those in their matched control subjects with normal renal function were approximately 1.3 (0.95, 1.86), 2.0 (1.62, 2.50), and 4.4 (3.11, 6.28), respectively. The geometric mean ratio (90% CI) of AUC0-t in subjects with mild, moderate, and severe renal impairment relative to those in their matched control subjects with normal renal function were approximately 1.4 (1.09, 1.73), 2.8 (2.27, 3.47), and 6.9 (5.21, 9.24), respectively [see Dosage and Administration (2.4)].

Table 4: Mean (SD) Cmax and AUC0-t of Carglumic Acid Following Single Oral Dose Administration of CARBAGLU 80 mg/kg or 40 mg/kg in Subjects with Renal Impairment and Matched Healthy Control Subjects with Normal Renal Function
PK Parameters | Normal Renal Function 1a: eGFR ≥90 mL/min/1.73m^2 (N=8) | Mild Renal Impairment: eGFR 60-89 mL/min/1.73m^2 (N=8) | Moderate Renal Impairment: eGFR 30-59 mL/min/1.73m^2 (N=8) | Normal Renal Function 1b: eGFR ≥90 mL/min/1.73m^2 (N=8) | Severe Renal Impairment: eGFR 15-29 mL/min/1.73m^2 (N=8)
PK Parameters | 80 mg/kg |  |  | 40 mg/kg
Cmax (ng/mL) | 2983 (552) | 4310 (1937) | 6129 (1854) | 1890 (901) | 8377 (3815)
AUC0-t (ng*hr/mL) | 28313 (6204) | 39545 (12109) | 79766 (19708) | 20212 (6186) | 143075 (55910)
Treatment groups 1a and 1b represent two separate matched control groups of healthy subjects with normal renal function.

Drug Interaction Studies
Based on in vitro studies, carglumic acid is not an inducer of CYP1A1/2, CYP2B6, CYP2C, and CYP3A4/5 enzymes, and not an inhibitor of CYP1A2, CYP2A6, CYP2B6, CYP2C8, CYP2C9, CYP2C19, CYP2D6, CYP2E1, and CYP3A4/5 enzymes.

Based on in vitro studies, carglumic acid is a substrate of the human OAT1 transporter. Carglumic acid is not a substrate of MDR1, BCRP, MATE1, MATE2-K, OAT1, OAT3, OATP1B1, OATP1B3, OCT1, and OCT2. Carglumic acid is not an inhibitor of human BSEP, BCRP, MDR1, MATE1, MATE2-K, OAT1, OAT3, OATP1B1, OATP1B3, OCT1, and OCT2 transporters.

13. NONCLINICAL TOXICOLOGY

13.1 Carcinogenesis, Mutagenesis, Impairment of Fertility

The carcinogenic potential of carglumic acid was assessed in a 2-year carcinogenicity study in rats. Carglumic acid was not tumorigenic at oral doses up to 1000 mg/kg/day (approximately 34 times the maximum reported human maintenance dose [100 mg/kg/day] based on AUC).

Carglumic acid was negative in the Ames test, chromosomal aberration assay in human lymphocytes, and the in vivo micronucleus assay in rats.

There were no effects on fertility or reproductive performance in female rats at oral doses up to 2000 mg/kg/day (approximately 38 times the maximum reported human maintenance dose [100 mg/kg/day] based on AUC). In a separate study, mating and fertility were unaffected in male rats at oral doses up to 1000 mg/kg/day (approximately 34 times the maximum reported human maintenance dose [100 mg/kg/day] based on AUC).

14. CLINICAL STUDIES

14.1 Acute and Chronic Hyperammonemia due to NAGS Deficiency

The efficacy of CARBAGLU in the treatment of acute and chronic hyperammonemia due to NAGS deficiency was evaluated in a retrospective case series of 23 NAGS deficiency patients treated with CARBAGLU over a median duration of 7.9 years (range 0.6 to 20.8 years). For acute treatment, patients received CARBAGLU at 100 mg/kg/day to 250 mg/kg/day orally administered in 2 to 4 divided doses. For maintenance treatment, the dosage was reduced over time based on plasma ammonia level and clinical response.

The baseline characteristics of the patient population are shown in Table 5.

Table 5: Baseline Characteristics of 23 NAGS Deficiency Patients Treated with CARBAGLU
 |  | Patients; N=23
Sex | Male | 14 (61%)
Sex | Female | 9 (39%)
Age at initiation of CARBAGLU therapy (years) | Mean (SD) | 2 (4)
Age at initiation of CARBAGLU therapy (years) | Min-Max | 0-13
Age groups at initiation of CARBAGLU therapy | <30 days | 9 (39%)
Age groups at initiation of CARBAGLU therapy | >30 days - 11 months | 9 (39%)
Age groups at initiation of CARBAGLU therapy | ≥1 - 13 years | 5 (22%)
NAGS gene mutations by DNA testing | Homozygous | 14 (61%)
NAGS gene mutations by DNA testing | Heterozygous | 4 (17%)
NAGS gene mutations by DNA testing | Not available | 5 (22%)
Patients current treatment status | On-going | 18 (78%)
 | Discontinued | 5 (22%)

The clinical and biochemical data in the 23-patient case series were retrospectively collected, unblinded and uncontrolled and preclude formal statistical testing. Short-term efficacy was evaluated using mean and median change in plasma ammonia levels from baseline to days 1 to 3. Persistence of the effect was evaluated using long-term mean and median change in plasma ammonia level. Of the 23 NAGS deficiency patients in the case series, 13 patients had documented plasma ammonia levels prior to CARBAGLU treatment and after long-term treatment with CARBAGLU and were evaluable. Table 5 summarizes the plasma ammonia levels at baseline, days 1 to 3 post-CARBAGLU treatment, and long-term CARBAGLU treatment (mean 8 years) in the 13 evaluable patients.

All 13 patients had increased plasma ammonia levels at baseline (mean 271 micromol/L; normal range: 5 to 50 micromol/L). By day 3 and with long-term treatment, normal plasma ammonia levels were attained (Table 6).

Table 6: Plasma Ammonia Levels in NAGS Deficiency Patients at Baseline and After Treatment with CARBAGLU
Timepoint | Patients (N = 13) | Ammonia level (micromol/L)
Baseline (prior to first dose of CARBAGLU) | N | 13
Baseline (prior to first dose of CARBAGLU) | Mean (SD) | 271 (359)
Baseline (prior to first dose of CARBAGLU) | Median | 157
Baseline (prior to first dose of CARBAGLU) | Range | 72-1428
Baseline (prior to first dose of CARBAGLU) | Missing Data | 0
Day 1 | N | 10
Day 1 | Mean (SD) | 181 (358)
Day 1 | Median | 65
Day 1 | Range | 25-1190
Day 1 | Missing Data | 3
Day 2 | N | 8
Day 2 | Mean (SD) | 69 (78)
Day 2 | Median | 44
Day 2 | Range | 11-255
Day 2 | Missing Data | 5
Day 3 | N | 5
Day 3 | Mean (SD) | 27 (11)
Day 3 | Median | 25
Day 3 | Range | 12-42
Day 3 | Missing Data | 8
Long-term treatment (mean duration 8 years; median duration 6 years; range 1-16 years based on last available value while on CARBAGLU treatment) | N | 13
Long-term treatment (mean duration 8 years; median duration 6 years; range 1-16 years based on last available value while on CARBAGLU treatment) | Mean (SD) | 23 (7)
Long-term treatment (mean duration 8 years; median duration 6 years; range 1-16 years based on last available value while on CARBAGLU treatment) | Median | 24
Long-term treatment (mean duration 8 years; median duration 6 years; range 1-16 years based on last available value while on CARBAGLU treatment) | Range | 9-34
 | Missing Data | 0

The mean plasma ammonia level at baseline and the decline that is observed after treatment with CARBAGLU in 13 evaluable patients with NAGS deficiency is illustrated in Figure 1.

Figure 1: Mean Plasma Ammonia in 13 Evaluable NAGS Deficiency Patients at Baseline and After Treatment with CARBAGLU

14.2 Acute Hyperammonemia due to PA and MMA

A randomized, double-blind, placebo-controlled, multicenter clinical trial evaluated the efficacy of CARBAGLU in the treatment of hyperammonemia in patients with PA and MMA (NCT01599286).

Eligible hyperammonemic episodes, defined as an admission to the hospital with a plasma ammonia level ≥ 70 micromol/L, were randomized 1:1 to receive either CARBAGLU or placebo for 7 days or until hospital discharge, whichever occurred earlier. All patients received standard of care, including a combination of protein restriction, intravenous glucose, insulin, and/or L-carnitine; the use of alternative pathway medications (e.g., sodium benzoate and medications with phenylacetate as an active metabolite) was prohibited. CARBAGLU was dosed orally at 150 mg/kg/day for patients ≤ 15 kg or 3.3 g/m^2/day for patients > 15 kg and was divided into 2 equal doses administered 12 hours apart by NG tube, G-tube, or oral syringe. Plasma ammonia testing was performed at pre-randomization and at post-dosing intervals of every 6 -12 hours for the first 48 hours and every day thereafter if the ammonia level was ≥ 50 micromol/L.

The efficacy evaluation was based on 90 hyperammonemic episodes (42 treated with CARBAGLU and 48 with placebo) in 24 patients (12 male and 12 female) with PA (n = 15) or MMA (n = 9). The median patient age was 8 years (range 4 days to 29 years). The primary endpoint was the time from the first dose of drug to the earlier of plasma ammonia level ≤ 50 micromol/L (normal range) or hospital discharge. The median time to reach the primary endpoint was 1.5 days in the CARBAGLU group compared to 2.0 days in the placebo group, a difference of 0.5 days (95% confidence interval: -1.2, 0.1), driven by an effect on plasma ammonia normalization. Throughout the first three days of treatment, a higher proportion of CARBAGLU-treated episodes reached the primary endpoint compared to placebo-treated episodes (Figure 2).

Figure 2: Episodes Reaching the Earlier of Plasma Ammonia Level ≤ 50 micromol/L or Hospital Discharge in Patients with PA or MMA Treated with CARBAGLU or Placebo for up to 7 days

16. HOW SUPPLIED/STORAGE AND HANDLING

How Supplied
CARBAGLU is a white and elongated 200 mg tablet for oral suspension, functionally scored with 3 lines for splitting into 4 equal portions, and coded "C" on one side.

CARBAGLU is supplied in a high-density polyethylene bottle with a child resistant polypropylene cap and desiccant unit. Each bottle contains either 5 or 60 tablets.

Bottle of 5 tablets: NDC 52276-312-05

Bottle of 60 tablets: NDC 52276-312-60

Storage
Store refrigerated at 2°C to 8°C (36°F to 46°F) in the original unopened bottle.

After first opening of the bottle:

- Store at room temperature between 15°C and 30°C (59°F and 86°F). Do not refrigerate.
- Keep the bottle tightly closed between openings in order to protect from moisture.
- Write the date of opening on the bottle.
- Do not use CARBAGLU after the expiration date stated on the bottle.
- Discard bottle one month after first opening.

17. PATIENT COUNSELING INFORMATION

Advise the patient to read the FDA-approved patient labeling (Instructions for Use).

Advise the patient or caregiver on the following:

Preparation and Administration [see Dosage and Administration (2.5)]

- Disperse CARBAGLU tablets in water. Do not swallow whole or crushed.
- Take CARBABLU immediately before meals or feedings.
- CARBAGLU tablets dispersed in water can be administered orally or via a nasogastric tube or gastrostomy tube as described in the Instructions for Use.

Storage [see How Supplied/Storage and Handling (16)]

- Store UNOPENED bottle in a refrigerator at 2°C to 8°C (36°F to 46°F).
- After first opening of the bottle: do not refrigerate, store at room temperature between 15°C and 30°C (59°F and 86°F). Keep the bottle tightly closed in order to protect from moisture. Write the date of opening on the bottle.
- Discard bottle one month after first opening. Do not use CARBAGLU after the expiration date stated on the bottle.

Pregnancy [see Use in Specific Populations (8.1)]
Advise women with NAGS deficiency who are exposed to CARBAGLU during pregnancy that there is a pregnancy surveillance program that monitors pregnancy outcomes.

This product's labeling may have been updated. For the most recent Prescribing Information, please visit www.recordatirarediseases.com/us or www.carbaglu.com.

Supplied by:
Recordati Rare Diseases
Puteaux, France

Licensed to and Distributed by:
Recordati Rare Diseases Inc.
Bridgewater, NJ 08807

Carbaglu® is a licensed trademark of Recordati Rare Diseases Inc.

PATIENT INFORMATION

INSTRUCTIONS FOR USE
CARBAGLU® (CAR-buh-gloo)
(carglumic acid)
Tablets for oral suspension

Important information:

- CARBAGLU tablets for oral suspension (CARBAGLU tablet) must be mixed in water before taking. CARBAGLU tablets should not be mixed in any other food or liquid.
- Do not swallow CARBAGLU tablets whole.
- Do not crush CARBAGLU tablets.
- Take CARBAGLU right before meals or feedings.
- The CARBAGLU tablet and water mixture has a slightly sour taste.

You may need to ask your healthcare provider or pharmacist for a medicine cup to measure the correct amount of water you will need to prepare the dose of CARBAGLU.

The CARBAGLU tablet has 3 lines used for splitting the tablet into 4 equal parts in order to get the prescribed dose. Ask your healthcare provider if you have any questions about how to split the tablet the right way or have any questions about the prescribed dose.

Taking CARBAGLU tablets by mouth using a cup:

Children and Adults

1. Add a minimum of 2.5 mL of water into a small cup for each CARBAGLU tablet, or each ½ or ¼ CARBAGLU tablet, needed for the prescribed dose. For example:
  - If the prescribed dose is 2 CARBAGLU tablets, add a minimum of 5 mL of water into the cup.
  - If the prescribed dose is 2 and a ¼ CARBAGLU tablets, add a minimum of 7.5 mL of water into the cup.
  - If the prescribed dose is 2 and a ½ CARBAGLU tablets, add a minimum of 7.5 mL of water into the cup.
  - Ask your healthcare provider if you are not sure of how much water you should use for the prescribed dose of CARBAGLU.
2. Place the prescribed number of CARBAGLU tablets into the water in the cup.
3. Carefully stir the CARBAGLU tablet and water mixture in the cup to avoid spilling the mixture. CARBAGLU tablets do not dissolve completely in water.
4. Swallow the CARBAGLU tablet and water mixture right away.
5. Pieces of the tablet may remain in the cup. Add more water to the cup to rinse the cup and swallow the mixture right away.
6. Repeat step 5 until there are no pieces of the tablet left in the cup.

Taking CARBAGLU tablets by mouth using an oral syringe:

Children

1. Add a minimum of 2.5 mL of water into a small cup for each CARBAGLU tablet, or each ½ or ¼ CARBAGLU tablet, needed for the prescribed dose. For example:
  - If the prescribed dose is 2 CARBAGLU tablets, add a minimum of 5 mL of water into the cup.
  - If the prescribed dose is 2 and a ¼ CARBAGLU tablets, add a minimum of 7.5 mL of water into the cup.
  - If the prescribed dose is 2 and a ½ CARBAGLU tablets, add a minimum of 7.5 mL of water into the cup.
  - Ask your healthcare provider if you are not sure of how much water you should use for the prescribed dose of CARBAGLU.
2. Place the prescribed number of CARBAGLU tablets into the water in the cup.
3. Carefully stir the CARBAGLU tablet and water mixture in the cup to avoid spilling the mixture. CARBAGLU tablets do not dissolve completely in water.
4. Draw up all of the CARBAGLU tablet and water mixture in the cup into an oral syringe.
5. Give your child the CARBAGLU tablet and water mixture right away by placing the tip of the oral syringe along the inner cheek of their mouth, on either the right or left side. Slowly push all the way down on the plunger to give the medicine.
6. Pieces of the tablet may remain in the oral syringe. Refill the oral syringe with a minimum of 1 mL to 2 mL of water and give your child the mixture right away.
7. Repeat step 6 until there are no pieces of the tablet left in the oral syringe.

Giving CARBAGLU tablets through a nasogastric (NG) or gastrostomy tube (G-tube):

Children and Adults

1. Add a minimum of 2.5 mL of water into a small cup for each CARBAGLU tablet, or each ½ or ¼ CARBAGLU tablet, needed for the prescribed dose. For example:
  - If the prescribed dose is 2 CARBAGLU tablets, add a minimum of 5 mL of water into the cup.
  - If the prescribed dose is 2 and a ¼ CARBAGLU tablets, add a minimum of 7.5 mL of water into the cup.
  - If the prescribed dose is 2 and a ½ CARBAGLU tablets, add a minimum of 7.5 mL of water into the cup.
  - Ask your healthcare provider if you are not sure of how much water you should use for the prescribed dose of CARBAGLU.
2. Place the prescribed number of CARBAGLU tablets into the water in the cup.
3. Carefully stir the CARBAGLU tablet and water mixture in the cup to avoid spilling the mixture. CARBAGLU tablets do not dissolve completely in water.
4. Draw up all of the CARBAGLU tablet and water mixture in the cup into a catheter-tip syringe.
5. Connect the catheter-tip syringe to the NG tube or G-tube.
6. Give the CARBAGLU tablet and water mixture through the NG tube or G-tube right away.
7. Pieces of the tablet may remain in the catheter-tip syringe or NG tube or G-tube.
8. Refill the catheter-tip syringe with 1 mL to 2 mL of water and flush the NG tube or G-tube right away.
9. Repeat step 8 until there are no pieces of the tablet left in the catheter-tip syringe or NG tube or G-tube.

How should I store CARBAGLU?

- Before opening, store CARBAGLU in a refrigerator between 36°F to 46°F (2°C to 8°C) in the bottle it comes in.
- After opening, store CARBAGLU at room temperature between 59°F to 86°F (15°C to 30°C). Do not store CARBAGLU in a refrigerator after opening.
  - Keep CARBAGLU tablets in a tightly closed bottle to protect the tablets from moisture.
  - Write the date the CARBAGLU bottle is opened on the bottle label. Throw away any unused tablets one month after opening the bottle.
- Do not use CARBAGLU tablets after the expiration date on the bottle.
- Keep CARBAGLU and all medicines out of the reach of children.

This Instructions for Use has been approved by the U.S. Food and Drug Administration.

Distributed by:

Recordati Rare Diseases Inc.
Bridgewater, NJ 08807

Issued: 1/2024

Carbaglu® is a licensed trademark of Recordati Rare Diseases

PACKAGING AND LABELING

NDC 52276-312-60
Carbaglu® 200 mg
carglumic acid
tablets for oral suspension
60 Tablets
Rx only
Before opening, store refrigerated at
2°C – 8°C (36°F – 46°F). Do not refrigerate.
Do not store above 30°C (86°F).
Discard one month after first opening
Date of first opening.
4022649 5/1344

NDC 52276-312-60
Carbaglu® 200 mg
carglumic acid
tablets for oral suspension
60 Tablets
Rx only
Disperse CARBAGLU tablets in water.
Do not swallow whole or crushed.
Supplied by:
Recordati Rare Diseases
Puteaux, France
Distributed by:
Recordati Rare Diseases Inc.
Lebanon, NJ 08833 USA
RECORDATI
RARE DISEASES
Group

NDC 52276-312-05
Carbaglu® 200 mg
carglumic acid
tablets for oral suspension
5 Tablets
Rx only
Before opening, store refrigerated at
2°C – 8°C (36°F – 46°F). Do not refrigerate.
Do not store above 30°C (86°F).
Discard one month after first opening
Date of first opening.
4022647 5/1142

NDC 52276-312-05
Carbaglu® 200 mg
carglumic acid
tablets for oral suspension
5 Tablets
Rx only
Disperse CARBAGLU tablets in water.
Do not swallow whole or crushed.
Supplied by:
Recordati Rare Diseases
Puteaux, France
Distributed by:
Recordati Rare Diseases Inc.
Lebanon, NJ 08833 USA
RECORDATI
RARE DISEASES
Group